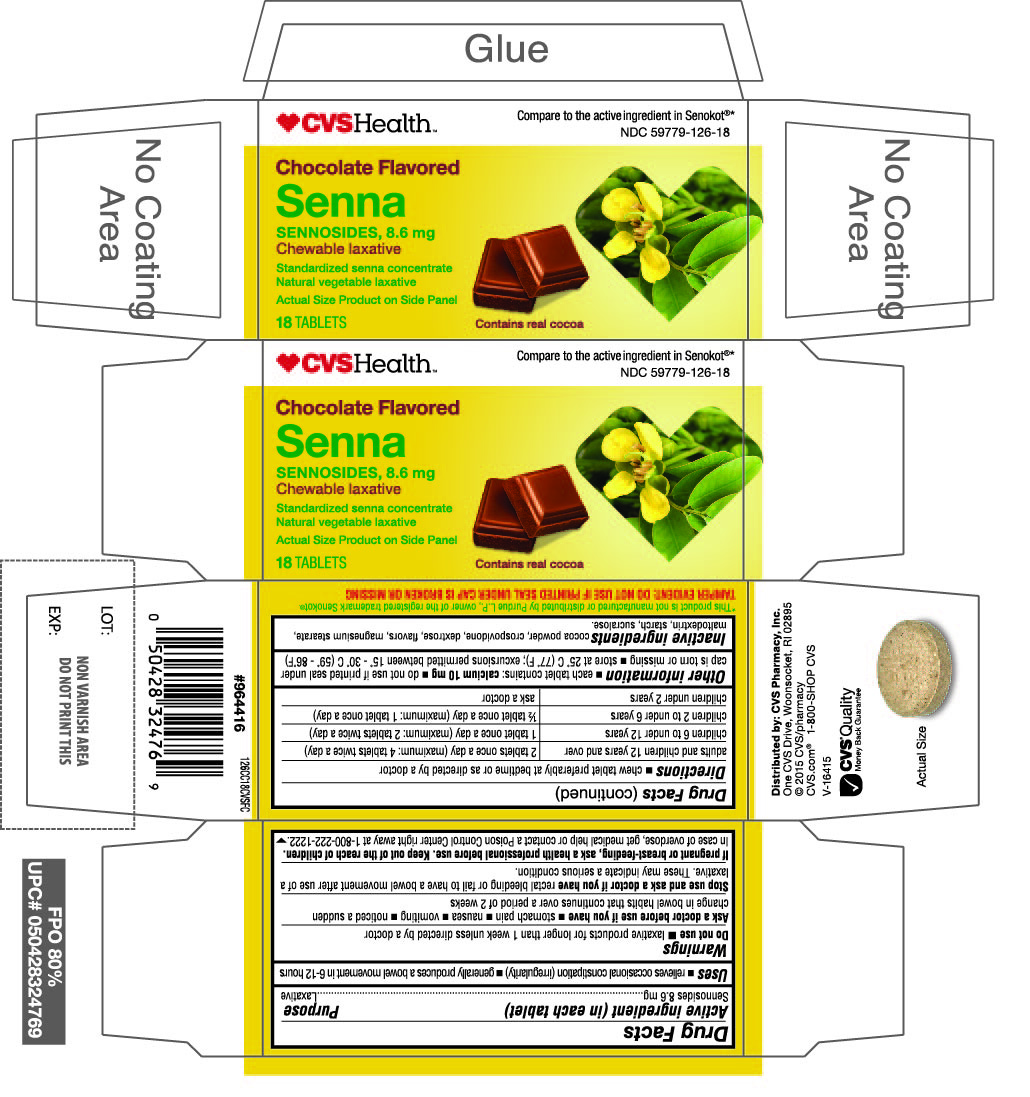 DRUG LABEL: Chocolate Flavored Senna
NDC: 69842-126 | Form: TABLET, CHEWABLE
Manufacturer: CVS Pharmacy,Inc.
Category: otc | Type: HUMAN OTC DRUG LABEL
Date: 20200818

ACTIVE INGREDIENTS: SENNOSIDES 8.6 mg/1 1
INACTIVE INGREDIENTS: COCOA; CROSPOVIDONE (15 MPA.S AT 5%); DEXTROSE, UNSPECIFIED FORM; MAGNESIUM STEARATE; MALTODEXTRIN; STARCH, CORN; SUCRALOSE

Chocolate Flavored Senna Sennosides, 8.6 mg Chewable laxative

Drug Facts
Active ingredient (in each tablet)

Sennosides 8.6 mg

Purpose

Laxative

Uses

- relieves occasional constipation (irregularity)
- generally produces a bowel movement in 6-12 hours

Warnings

Do not use

- laxative products for longer than 1 week unless directed by a doctor

Ask a doctor before use if you have

- stomach pain
- nausea
- vomiting
- noticed a sudden change in bowel habits that continues over a period of 2 weeks

Stop use and ask a doctor if you have rectal bleeding or fail to have a bowel movement after use of a laxative. These may indicate a serious condition.

PREGNANCY OR BREAST FEEDING

If pregnant or breast-feeding, ask a health professional before use.

Keep out of reach of children.

In case of overdose, get medical help or contact a Poison Control Center right away at 1-800-222-1222.

Directions

- chew tablet preferably at bedtime or as directed by a doctor

age | starting dosage | maximum dosage
adults and children 12 years of age and over | 2 tablets once a day | 4 tablets twice a day
children 6 to under 12 years | 1 tablet once a day | 2 tablets twice a day
children 2 to under 6 years | 1/2 tablet once a day | 1 tablet once a day
children under 2 years | ask a doctor | ask a doctor

Other Information

- each tablet contains: calcium 10 mg
- do not use if printed seal under cap is torn or missing
- store at 25°C (77°F); excursions permitted between 15°-30°C (59°-86°F)

Inactive ingredients

cocoa powder, crospovidone, dextrose, flavors, magnesium stearate, maltodextrin, starch, sucralose

CVS Health™

Compare to the active ingredient in Senokot®

Chocolate Flavored

Senna

Sennosides, 8.6 mg

Chewable laxative

Standardized senna concentrate

Natural vegetable laxative

18 TABLETS

Contains real cocoa

This product is not manufactured or distributed by Purdue L.P. owner of the registered trademark Senokot®

TAMPER EVIDENT: DO NOT USE IF PRINTED SEAL UNDER CAP IS BROKEN OR MISSING

Distributed by: CVS Pharmacy, Inc

One CVS Drive, Woonsocket, RI 02895

2015 CVS/Pharmacy

CVS.com

1-800-SHOP CVS